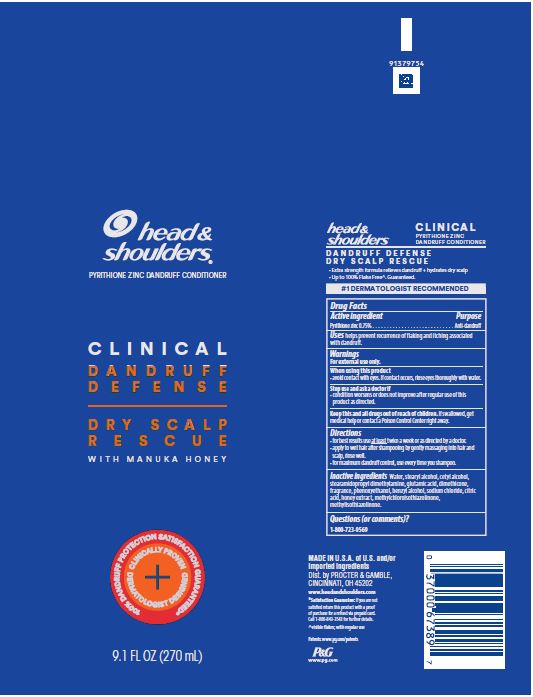 DRUG LABEL: Head and Shoulders Clinical Dandruff Defense Dry Scalp Rescue
NDC: 69423-568 | Form: LOTION
Manufacturer: The Procter & Gamble Manufacturing Company
Category: otc | Type: HUMAN OTC DRUG LABEL
Date: 20251218

ACTIVE INGREDIENTS: PYRITHIONE ZINC 0.75 g/100 mL
INACTIVE INGREDIENTS: METHYLCHLOROISOTHIAZOLINONE; METHYLISOTHIAZOLINONE; STEARAMIDOPROPYL DIMETHYLAMINE; GLUTAMIC ACID; PHENOXYETHANOL; BENZYL ALCOHOL; CITRIC ACID MONOHYDRATE; HONEY; SODIUM CHLORIDE; STEARYL ALCOHOL; CETYL ALCOHOL; WATER; DIMETHICONE

Head and Shoulders®
Clinical Dandruff Defense Dry Scalp Rescue

Drug Facts

Active ingredient

Pyrithione zinc .75%

Purpose

Anti-dandruff

Uses

helps prevent recurrence of flaking and itching associated with dandruff.

Warnings

For external use only.

When using this product

- avoid contact with eyes. If contact occurs, rinse eyes thoroughly with water.

Stop use and ask a doctor if

- condition worsens or does not improve after regular use of this product as directed.

KEEP OUT OF REACH OF CHILDREN

Keep this and all drugs out of reach of children. If swallowed, get medical help or contact a Poison Control Center right away.

Directions

- for best results use at least twice a week or as directed by a doctor.
- apply to wet hair after shampooing by gently massaging into hair and scalp, rinse well.
- for maximum dandruff control, use every time you shampoo.

Inactive ingredients

Water, stearyl alcohol, cetyl alcohol, stearamidopropyl dimethylamine, glutamic acid, dimethicone, fragrance, phenoxyethanol, benzyl alcohol, sodium chloride, citric acid, honey extract,methylchloroisothiazolinone, methylisothiazolinone.

Questions (or comments)?

1-800-723-9569

Dist. by PROCTER & GAMBLE,
CINCINNATI, OH 45202

PRINCIPAL DISPLAY PANEL - TUBE LABEL

head &

shoulders ®
pyrithione zinc dandruff conditioner

Clinical

Dandruff

Defense

Dry Scalp

Rescue

with Manuka Honey

100% DANDRUFF PROTECTION SATISFACTION GUARANTEED*

9.1 FL OZ (270 mL)